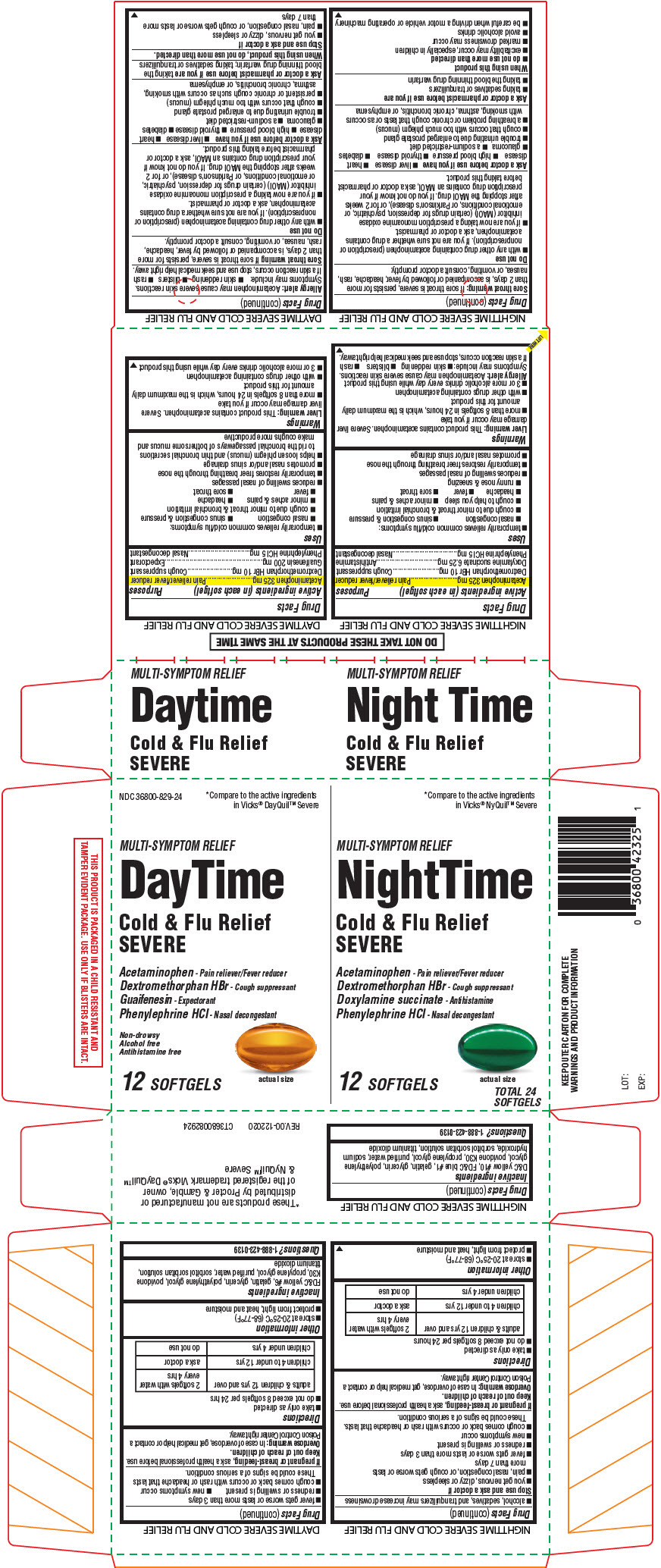 DRUG LABEL: Cold and Flu Severe Daytime/Nighttime
NDC: 36800-746 | Form: KIT | Route: ORAL
Manufacturer: TOPCO ASSOCIATES LLC
Category: otc | Type: HUMAN OTC DRUG LABEL
Date: 20210312

ACTIVE INGREDIENTS: ACETAMINOPHEN 325 mg/1 1; DEXTROMETHORPHAN HYDROBROMIDE 10 mg/1 1; GUAIFENESIN 200 mg/1 1; PHENYLEPHRINE HYDROCHLORIDE 5 mg/1 1; ACETAMINOPHEN 325 mg/1 1; DEXTROMETHORPHAN HYDROBROMIDE 10 mg/1 1; DOXYLAMINE SUCCINATE 6.25 mg/1 1; PHENYLEPHRINE HYDROCHLORIDE 5 mg/1 1
INACTIVE INGREDIENTS: FD&C YELLOW NO. 6; GELATIN, UNSPECIFIED; GLYCERIN; POLYETHYLENE GLYCOL, UNSPECIFIED; POVIDONE, UNSPECIFIED; PROPYLENE GLYCOL; WATER; TITANIUM DIOXIDE; D&C YELLOW NO. 10; FD&C BLUE NO. 1; GELATIN, UNSPECIFIED; GLYCERIN; POLYETHYLENE GLYCOL, UNSPECIFIED; POVIDONE, UNSPECIFIED; PROPYLENE GLYCOL; WATER; SODIUM HYDROXIDE; TITANIUM DIOXIDE

Cold and Flu Severe Daytime/Nighttime

DAYTIME SEVERE COLD AND FLU RELIEF

Drug Facts

ACTIVE INGREDIENT

PURPOSE

Active ingredients (in each softgel) | Purposes
Acetaminophen 325 mg | Pain reliever/fever reducer
Dextromethorphan HBr 10 mg | Cough suppressant
Guaifenesin 200 mg | Expectorant
Phenylephrine HCl 5 mg | Nasal decongestant

Uses

- temporarily relieves common cold/flu symptoms:
  - nasal congestion
  - sinus congestion & pressure
  - cough due to minor throat & bronchial irritation
  - minor aches & pains
  - headache
  - fever
  - sore throat
- reduces swelling of nasal passages
- temporarily restores freer breathing through the nose
- promotes nasal and/or sinus drainage
- helps loosen phlegm (mucus) and thin bronchial secretions to rid the bronchial passageways of bothersome mucus and make coughs more productive

Warnings

Liver warning

This product contains acetaminophen. Severe liver damage may occur if you take

- more than 8 softgels in 24 hours, which is the maximum daily amount for this product
- with other drugs containing acetaminophen
- 3 or more alcoholic drinks every day while using this product

Allergy alert

Acetaminophen may cause severe skin reactions. Symptoms may include:

- skin reddening
- blisters
- rash

If a skin reaction occurs, stop use and seek medical help right away.

Sore throat warning

If sore throat is severe, persists for more than 2 days, is accompanied or followed by fever, headache, rash, nausea, or vomiting, consult a doctor promptly.

Do not use

- with any other drug containing acetaminophen (prescription or nonprescription). If you are not sure whether a drug contains acetaminophen, ask a doctor or pharmacist.
- if you are now taking a prescription monoamine oxidase inhibitor (MAOI) (certain drugs for depression, psychiatric, or emotional conditions, or Parkinson's disease), or for 2 weeks after stopping the MAOI drug. If you do not know if your prescription drug contains an MAOI, ask a doctor or pharmacist before taking this product.

Ask a doctor before use if you have

- liver disease
- heart disease
- high blood pressure
- thyroid disease
- diabetes
- glaucoma
- a sodium-restricted diet
- trouble urinating due to enlarged prostate gland
- cough that occurs with too much phlegm (mucus)
- persistent or chronic cough such as occurs with smoking, asthma, chronic bronchitis, or emphysema

Ask a doctor or pharmacist before use if you are taking the blood thinning drug warfarin; taking sedatives or tranquilizers

When using this product, do not use more than directed.

Stop use and ask a doctor if

- you get nervous, dizzy or sleepless
- pain, nasal congestion, or cough gets worse or lasts more than 7 days
- fever gets worse or lasts more than 3 days
- redness or swelling is present
- new symptoms occur
- cough comes back or occurs with rash or headache that lasts

These could be signs of a serious condition.

PREGNANCY OR BREAST FEEDING

If pregnant or breast-feeding, ask a health professional before use.

Overdose warning

In case of overdose, get medical help or contact a Poison Control Center right away.

Directions

- take only as directed
- do not exceed 8 softgels per 24 hrs

adults & children 12 yrs and over | 2 softgels with water every 4 hrs
children 4 to under 12 yrs | ask a doctor
children under 4 yrs | do not use

Other information

- store at 20-25°C (68-77°F)
- protect from light, heat and moisture

Inactive ingredients

FD&C yellow #6, gelatin, glycerin, polyethylene glycol, povidone K30, propylene glycol, purified water, sorbitol sorbitan solution, titanium dioxide

Questions?

1-888-423-0139

NIGHTTIME SEVERE COLD AND FLU RELIEF

Drug Facts

ACTIVE INGREDIENT

PURPOSE

Active ingredients (in each softgel) | Purposes
Acetaminophen 325 mg | Pain reliever/fever reducer
Dextromethorphan HBr 10 mg | Cough suppressant
Doxylamine succinate 6.25 mg | Antihistamine
Phenylephrine HCl 5 mg | Nasal decongestant

Uses

- temporarily relieves common cold/flu symptoms:
  - nasal congestion
  - sinus congestion & pressure
  - cough due to minor throat & bronchial irritation
  - cough to help you sleep
  - minor aches & pains
  - headache
  - fever
  - sore throat
  - runny nose & sneezing
- reduces swelling of nasal passages
- temporarily restores freer breathing through the nose
- promotes nasal and/or sinus drainage

Warnings

Liver warning

This product contains acetaminophen. Severe liver damage may occur if you take

- more than 8 softgels in 24 hours, which is the maximum daily amount for this product
- with other drugs containing acetaminophen
- 3 or more alcoholic drinks every day while using this product

Allergy alert

Acetaminophen may cause severe skin reactions. Symptoms may include:

- skin reddening
- blisters
- rash

If a skin reaction occurs, stop use and seek medical help right away.

Sore throat warning

If sore throat is severe, persists for more than 2 days, is accompanied or followed by fever, headache, rash, nausea, or vomiting, consult a doctor promptly.

Do not use

- with any other drug containing acetaminophen (prescription or nonprescription). If you are not sure whether a drug contains acetaminophen, ask a doctor or pharmacist.
- if you are now taking a prescription monoamine oxidase inhibitor (MAOI) (certain drugs for depression, psychiatric, or emotional conditions, or Parkinson's disease), or for 2 weeks after stopping the MAOI drug. If you do not know if your prescription drug contains an MAOI, ask a doctor or pharmacist before taking this product.

Ask a doctor before use if you have

- liver disease
- heart disease
- high blood pressure
- thyroid disease
- diabetes
- glaucoma
- a sodium-restricted diet
- trouble urinating due to enlarged prostate gland
- cough that occurs with too much phlegm (mucus)
- a breathing problem or chronic cough that lasts or as occurs with smoking, asthma, chronic bronchitis, or emphysema

Ask a doctor or pharmacist before use if you are

- taking sedatives or tranquilizers
- taking the blood thinning drug warfarin

When using this product

- do not use more than directed
- excitability may occur, especially in children
- marked drowsiness may occur
- avoid alcoholic drinks
- be careful when driving a motor vehicle or operating machinery
- alcohol, sedatives, and tranquilizers may increase drowsiness

Stop use and ask a doctor if

- you get nervous, dizzy or sleepless
- pain, nasal congestion, or cough gets worse or lasts more than 7 days
- fever gets worse or lasts more than 3 days
- redness or swelling is present
- new symptoms occur
- cough comes back or occurs with rash or headache that lasts.

These could be signs of a serious condition.

PREGNANCY OR BREAST FEEDING

If pregnant or breast-feeding, ask a health professional before use.

Overdose warning

In case of overdose, get medical help or contact a Poison Control Center right away.

Directions

- take only as directed
- do not exceed 8 softgels per 24 hours

adults & children 12 yrs and over | 2 softgels with water every 4 hrs
children 4 to under 12 yrs | ask a doctor
children under 4 yrs | do not use

Other information

- store at 20-25°C (68-77°F)
- protect from light, heat and moisture

Inactive ingredients

D&C yellow #10, FD&C blue #1, gelatin, glycerin, polyethylene glycol, povidone K30, propylene glycol, purified water, sodium hydroxide, sorbitol sorbitan solution, titanium dioxide

Questions?

1-888-423-0139

PRINCIPAL DISPLAY PANEL - Kit Carton

NDC 36800-829-24

*Compare to the active ingredients
in Vicks® DayQuil™ Severe

MULTI-SYMPTOM RELIEF

DayTime

Cold & Flu Relief
SEVERE

Acetaminophen - Pain reliever/Fever reducer
Dextromethorphan HBr - Cough suppressant
Guaifenesin - Expectorant
Phenylephrine HCl - Nasal decongestant

Non-drowsy
Alcohol free
Antihistamine free

actual size

12 SOFTGELS

*Compare to the active ingredients
in Vicks® NyQuil™ Severe

MULTI-SYMPTOM RELIEF

NightTime

Cold & Flu Relief
SEVERE

Acetaminophen - Pain reliever/Fever reducer
Dextromethorphan HBr - Cough suppressant
Doxylamine succinate - Antihistamine
Phenylephrine HCl - Nasal decongestant

actual size

12 SOFTGELS

TOTAL 24
SOFTGELS